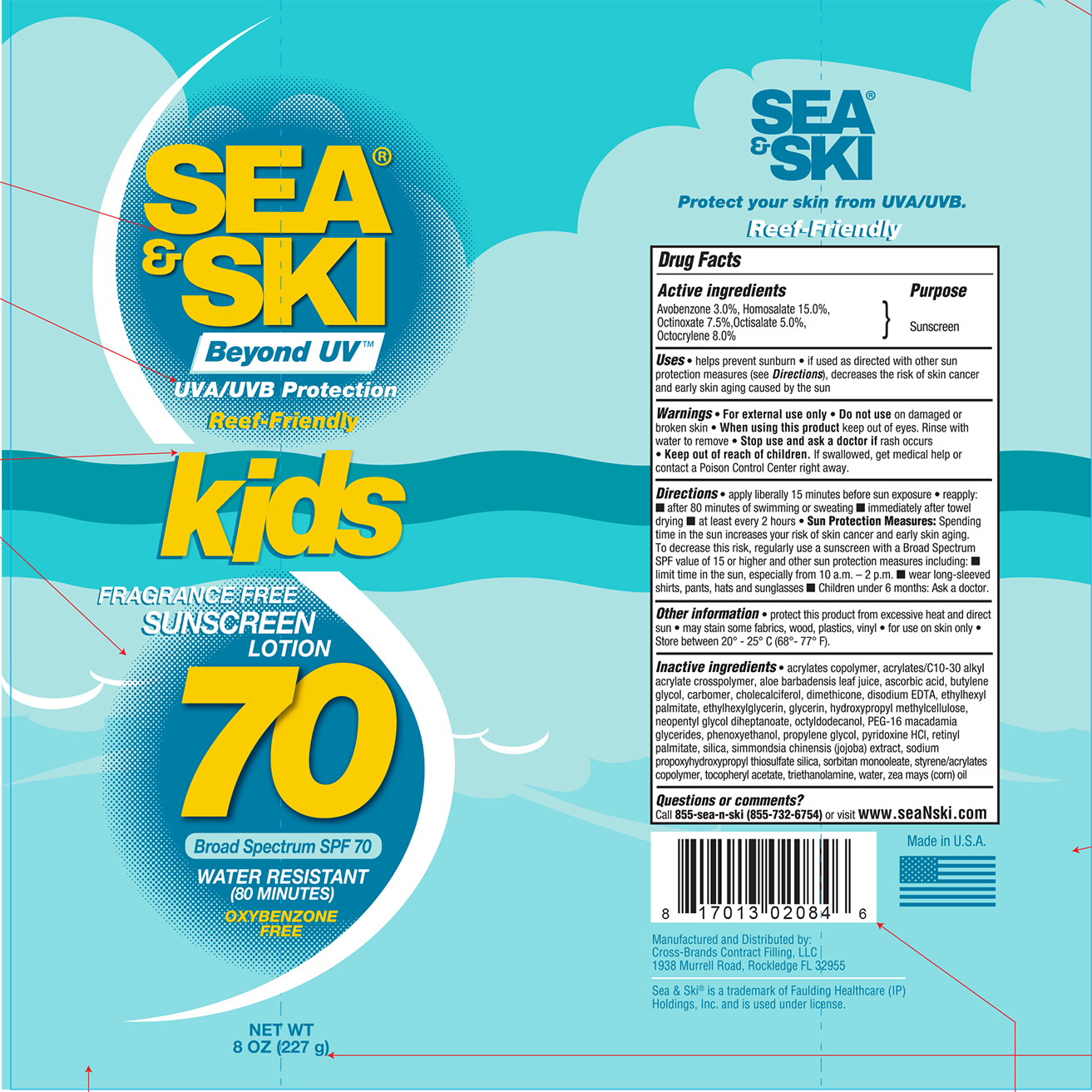 DRUG LABEL: Sea and Ski SPF 70 Kids
NDC: 73440-2084 | Form: LOTION
Manufacturer: Cross-Brands Contract Filling
Category: otc | Type: HUMAN OTC DRUG LABEL
Date: 20210219

ACTIVE INGREDIENTS: AVOBENZONE 6.81 g/227 g; HOMOSALATE 34.05 g/227 g; OCTISALATE 11.35 g/227 g; OCTOCRYLENE 18.16 g/227 g; OCTINOXATE 17.03 g/227 g
INACTIVE INGREDIENTS: WATER 106.5 g/227 g

Sea&Ski SPF 70 Kids 8oz